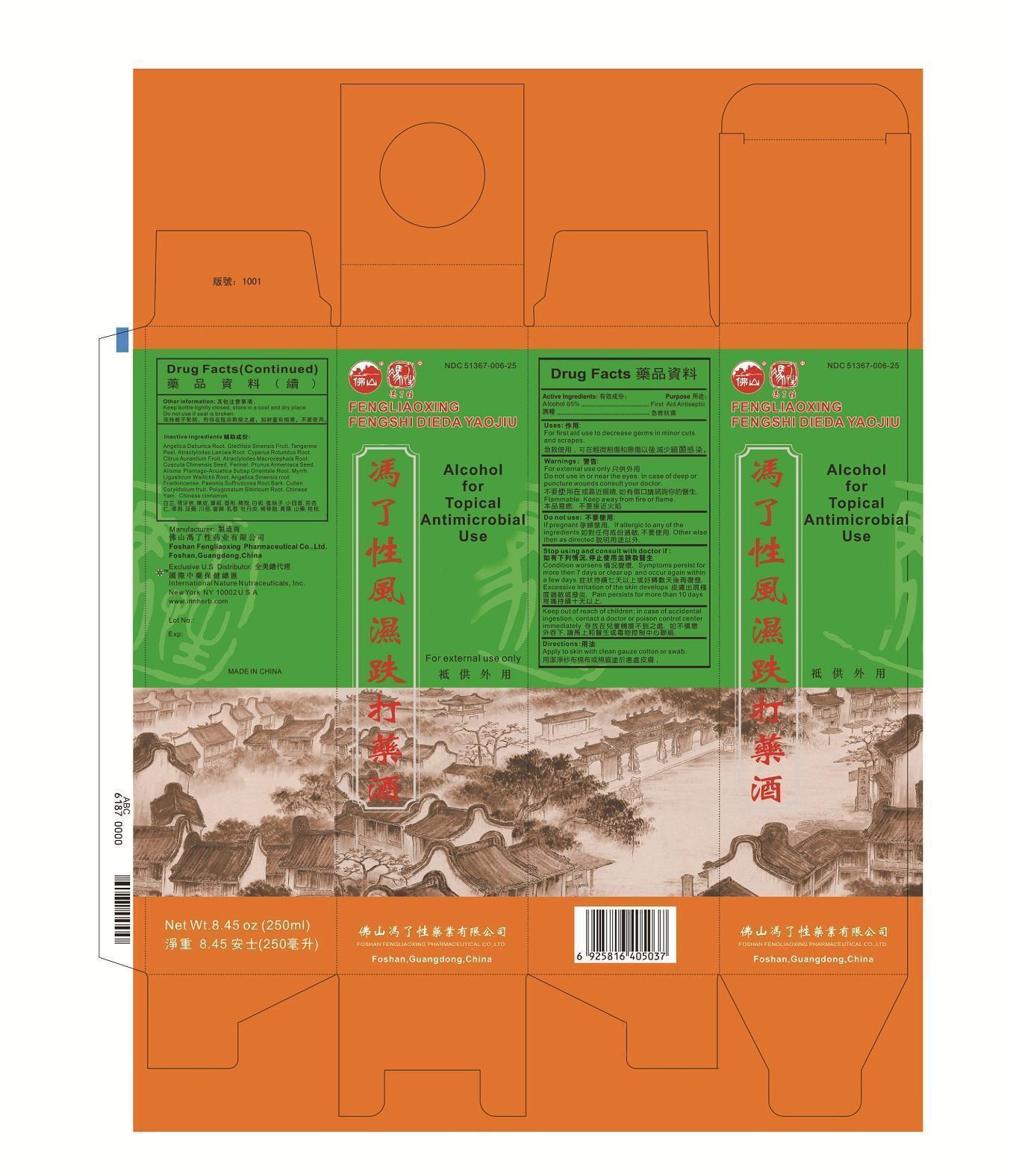 DRUG LABEL: Fengliaoxing Fengshi Dieda Yaojiu
NDC: 51367-006 | Form: LIQUID
Manufacturer: International Nature Nutraceuticals
Category: otc | Type: HUMAN OTC DRUG LABEL
Date: 20130311

ACTIVE INGREDIENTS: ALCOHOL 128.21 g/1 1
INACTIVE INGREDIENTS: ANGELICA DAHURICA ROOT; GLEDITSIA SINENSIS FRUIT; TANGERINE PEEL; ATRACTYLODES LANCEA ROOT; CYPERUS ROTUNDUS ROOT; CITRUS AURANTIUM FRUIT, IMMATURE; ATRACTYLODES MACROCEPHALA ROOT; CUSCUTA CHINENSIS SEED; FENNEL; PRUNUS ARMENIACA SEED; ALISMA PLANTAGO-AQUATICA SUBSP. ORIENTALE ROOT; MYRRH; LIGUSTICUM WALLICHII ROOT; ANGELICA SINENSIS ROOT; FRANKINCENSE; PAEONIA SUFFRUTICOSA ROOT BARK; CULLEN CORYLIFOLIUM FRUIT; POLYGONATUM SIBIRICUM ROOT; CHINESE YAM; CHINESE CINNAMON

Drug Facts

Active Ingredients:

Alcohol 65%

Uses

For first aid use to decrease germs in minor cuts and scrapes.

Warning:

For external use only

Do not use in or near the eyes. In case of deep or puncture wounds counsult your doctor.

Flammable. Keep away from fire or flame.

Do not use:

If pregnant. If allergic to any of the ingerdients.

Otherwise then as directed

Stop using and consult with doctor if:

Condition worsens. Symptoms persist for more then 7 days or clear up and occur again within a few days. Excessive irritation of the skin develops. Pain persists for more than 10 days.

Keep out of reach of children.

In case of accidental ingestion, contact a doctor or poision control center immediately.

Directions:

Apply to skin with clean guaze cotton or swab.

Other information:

Keep bottle tightly closed.

Store in a cool and dry place.

Do not use if seal is broken.

Inactive Ingredients

白芷 Angelica dahurica root.猪牙皂 Gleditsia Sinensis Fruit 陳皮。 Tangerine peel 苍朮。 Atractylodes lancea root. 香附 cyperus rotundus root. 枳壳 Citrus Aurantium Fruit, Immature. 白朮。 Atractylodes macrocephala root. 菟丝子。Cuscuta chinensis seed. 小茴香 Fennel. 苦杏仁。 Prunus armeniaca seed. 泽泻 Alisma Plantago-Aouatica Subsp. Orientale Root 没药。 Myrrh 川芎。 Ligusticum Wallichii root. 当归。 Angelica sinensis root. 乳香。 Frankincense 牡丹皮 Paeonia Suffruticosa Root Bark 补骨脂 Cullen Corylifolium Fruit 黃精。 Polygonatum Sibiricum Root. 山药。 Chinese Yam 桂枝。 Chinese Cinnamon